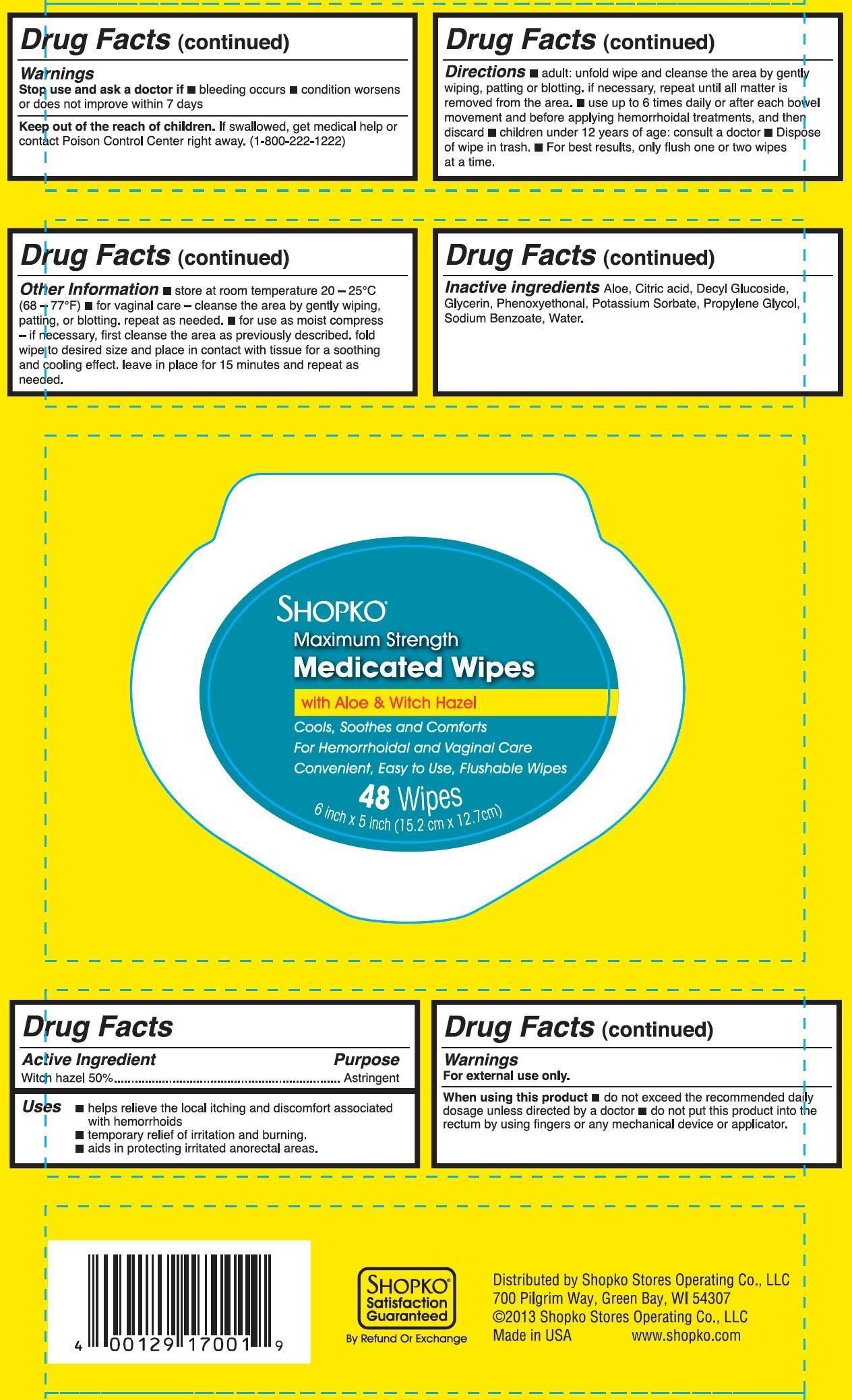 DRUG LABEL: SHOPKO Maximum Strength Medicated
NDC: 37012-121 | Form: CLOTH
Manufacturer: Shopko Stores Operating Co., LLC.
Category: otc | Type: HUMAN OTC DRUG LABEL
Date: 20130716

ACTIVE INGREDIENTS: WITCH HAZEL 50 g/100 g
INACTIVE INGREDIENTS: WATER; GLYCERIN; PROPYLENE GLYCOL; DECYL GLUCOSIDE; CITRIC ACID MONOHYDRATE; PHENOXYETHANOL; SODIUM BENZOATE; ALOE ARBORESCENS LEAF

SHOPKO Maximum Strength Medicated wipes

Active Ingredient

Witch hazel 50%

Purpose

Astringent

Uses

- helps relieve the local itching and disconfort associated with hemorrhoids
- temporary relief of irritation and burning.
- aids in protecting irritated anorectal areas.

Warnings

For external use only.

When using this product

- do not exceed the recommended daily dosage unless directed by a doctor
- do not put this product into the rectum by using fingers or any mechanical device or applicator.

Stop use and ask a doctor if

- bleeding occurs
- condition worsens or does not improve within 7 days

Keep out of reach of children

If swallowed, get medical help or contact a Poison Control Center right away.(1-800-222-1222)

Directions

- adult: unfold wipe and cleanse the area by gently wiping, patting or blotting. If necessary, repeat until all matter is removed from the area.
- use up to 6 times daily or after each bowel movement and before applying hemorrhoidal treatments, and then discard
- Dispose of wipe in trash.
- For best results, only flush one or two wipes at a time.

Other information

- store at room temperature 20-25°C (68-77°F)
- for vaginal care - cleanse the area by gently wiping, patting, or blotting. Repeat as needed.
- for use as moist compress - if necessary, first cleanse the area as previously described. Fold wipe to desire size and place in contact with tissue for a soothing and cooling effect. Leave in place for 15 minutes and repeat as needed.

Inactive Ingredients

Aloe, citric acid, Decyl Glucoside, Glycerin, Phenoxyethanol, Potassium Sorbate, Propylene Glycol, Sodium Benzoate, Water.

Principal Display Panel

SHOPKO

Maximum Strength

Medicated Wipes

with Aloe and Witch Hazel

Cools, Soothes and Cofmorts

For Hemorrhoidal and vaginal Care

Convenient, Easy to use, Flushable Wipes

48 Wipes

6 in. x 5 in. (15.2 cm x 12.7 cm)